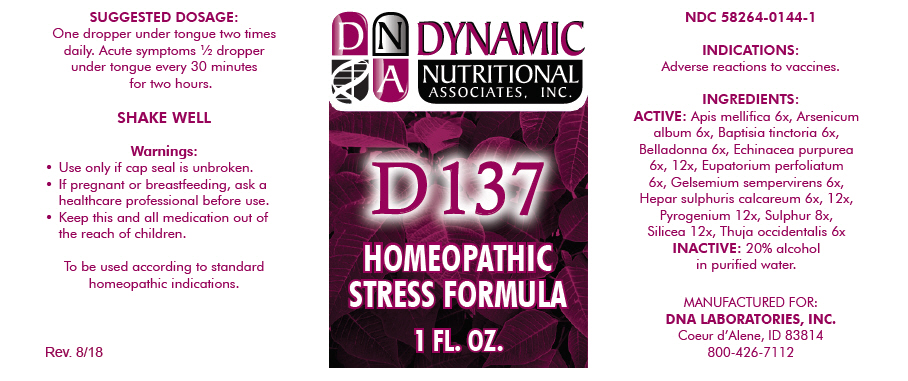 DRUG LABEL: D-137
NDC: 58264-0144 | Form: SOLUTION
Manufacturer: DNA Labs, Inc.
Category: homeopathic | Type: HUMAN OTC DRUG LABEL
Date: 20250113

ACTIVE INGREDIENTS: APIS MELLIFERA 6 [hp_X]/1 mL; ARSENIC TRIOXIDE 6 [hp_X]/1 mL; BAPTISIA TINCTORIA 6 [hp_X]/1 mL; ATROPA BELLADONNA 6 [hp_X]/1 mL; ECHINACEA PURPUREA 6 [hp_X]/1 mL; EUPATORIUM PERFOLIATUM WHOLE 6 [hp_X]/1 mL; GELSEMIUM SEMPERVIRENS WHOLE 6 [hp_X]/1 mL; CALCIUM SULFIDE 6 [hp_X]/1 mL; RANCID BEEF 12 [hp_X]/1 mL; SULFUR 8 [hp_X]/1 mL; SILICON DIOXIDE 12 [hp_X]/1 mL; THUJA OCCIDENTALIS LEAFY TWIG 6 [hp_X]/1 mL
INACTIVE INGREDIENTS: ALCOHOL; WATER

D-137

NDC 58264-0144-1

INDICATIONS

PURPOSE

Adverse reactions to vaccines.

INGREDIENTS

ACTIVE

Apis mellifica 6x, Arsenicum album 6x, Baptisia tinctoria 6x, Belladonna 6x, Echinacea purpurea 6x, 12x, Eupatorium perfoliatum 6x, Gelsemium sempervirens 6x, Hepar sulphuris calcareum 6x, 12x, Pyrogenium 12x, Sulphur 8x, Silicea 12x, Thuja occidentalis 6x

INACTIVE

20% alcohol in purified water.

SUGGESTED DOSAGE

One dropper under tongue two times daily. Acute symptoms ½ dropper under tongue every 30 minutes for two hours.

STORAGE AND HANDLING

SHAKE WELL

Warnings

- Use only if cap seal is unbroken.

PREGNANCY OR BREAST FEEDING

- If pregnant or breastfeeding, ask a healthcare professional before use.

KEEP OUT OF REACH OF CHILDREN

- Keep this and all medication out of the reach of children.

To be used according to standard homeopathic indications.

PRINCIPAL DISPLAY PANEL - 1 FL. OZ. Bottle Label

DYNAMIC
NUTRITIONAL
ASSOCIATES, INC.

D 137

HOMEOPATHIC
STRESS FORMULA

1 FL. OZ.